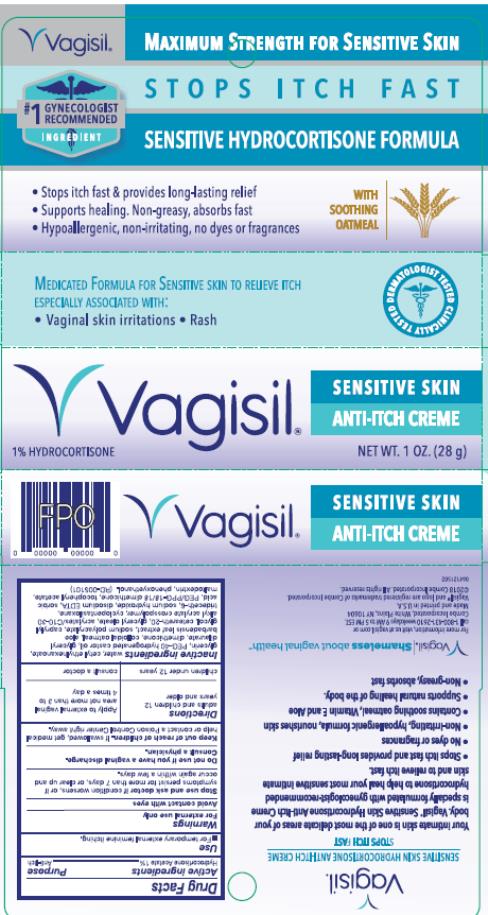 DRUG LABEL: Vagisil Anti-Itch Creme Maximum Strength Sensitive Skin Formula
NDC: 11509-5101 | Form: CREAM
Manufacturer: Combe Incorporated
Category: otc | Type: HUMAN OTC DRUG LABEL
Date: 20200420

ACTIVE INGREDIENTS: HYDROCORTISONE ACETATE 280 mg/28 g
INACTIVE INGREDIENTS: WATER; CETYL ETHYLHEXANOATE; GLYCERIN; POLYOXYL 40 HYDROGENATED CASTOR OIL; GLYCERYL DILAURATE; DIMETHICONE; OATMEAL; ALOE VERA LEAF; SODIUM POLYACRYLATE (2500000 MW); CAPRYLYL GLYCOL; POLYOXYL 20 CETOSTEARYL ETHER; GLYCERYL OLEATE; CARBOMER INTERPOLYMER TYPE A (55000 CPS); CYCLOMETHICONE 5; TRIDECETH-6; SODIUM HYDROXIDE; EDETATE DISODIUM; SORBIC ACID; PEG/PPG-18/18 DIMETHICONE; ALPHA-TOCOPHEROL ACETATE; MALTODEXTRIN; PHENOXYETHANOL

Vagisil Anti-Itch Crème Maximum Strength, Sensitive Skin Formula

Vagisil Sensitive Skin Anti-Itch Creme

Drug Facts

Active ingredients

Hydrocortisone Acetate 1%

Purpose

Anti-itch

Use

For temporary external feminine itching.

Warnings

For external use only

Avoid contact with eyes

Stop use and ask a doctor if

condition worsens, or if symptoms persist for more than 7 days, or clear up and occur again within a few days.

Do not use if

you have a vaginal discharge. Consult a physician.

Keep out of reach of children.

If swallowed, get medical help or contact a Poison Control Center right away.

Directions

adults and children 12 years and older | Apply to external vaginal area not more than 3 to 4 times a day
children under 12 years | consult a doctor

Inactive ingredients:

water, cetyl ethylhexanoate, glycerin, PEG-40 hydrogenated castor oil, glyceryl dilaurate, dimethicone, colloidal oatmeal, aloe barbadensis leaf extract, sodium polyacrylate, caprylyl glycol, ceteareth-20, glyceryl oleate, acrylates/C10-30 alkyl acrylate crosspolymer, cyclopentasiloxane, trideceth-6, sodium hydroxide, disodium EDTA, sorbic acid, PEG/PPG-18/18 dimethicone, tocopheryl acetate, maltodextrin, phenoxyethanol.

PRINCIPAL DISPLAY PANEL

Vagisil Sensitive Skin Anti-Itch Creme, 1% Hydrocortisone
Net. Wt. 1 oz. (28 g)